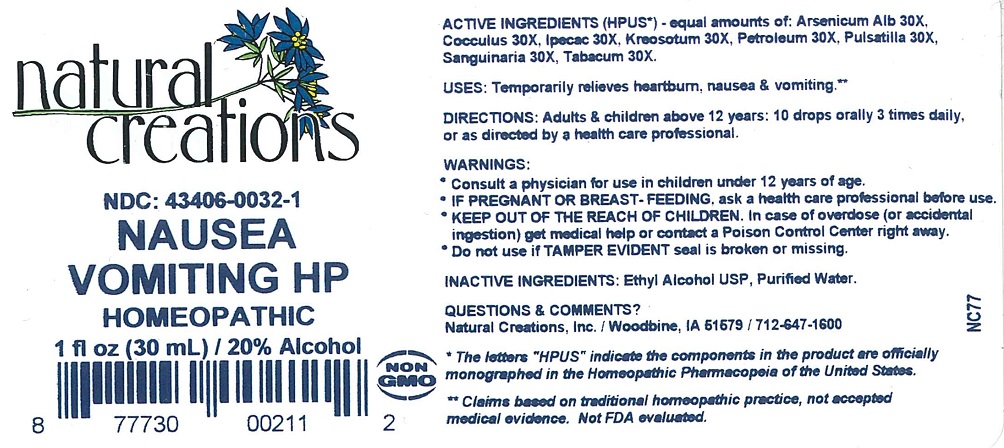 DRUG LABEL: NAUSEA VOMITING HP
NDC: 43406-0032 | Form: LIQUID
Manufacturer: Natural Creations, Inc.
Category: homeopathic | Type: HUMAN OTC DRUG LABEL
Date: 20251216

ACTIVE INGREDIENTS: ARSENIC TRIOXIDE 30 [hp_X]/1 mL; ANAMIRTA COCCULUS SEED 30 [hp_X]/1 mL; IPECAC 30 [hp_C]/1 mL; WOOD CREOSOTE 30 [hp_X]/1 mL; KEROSENE 30 [hp_X]/1 mL; PULSATILLA VULGARIS 30 [hp_X]/1 mL; SANGUINARIA CANADENSIS ROOT 30 [hp_X]/1 mL; TOBACCO LEAF 30 [hp_X]/1 mL
INACTIVE INGREDIENTS: ALCOHOL; WATER

NAUSEA VOMITING HP

ACTIVE INGREDIENT

Active Ingredients (HPUS*) - equal amounts of: Aresnicum Album 30X, Cocculus Indicus 30X, Ipecacuanha 30X, Kreosotum 30X, Petroleum 30X, Pulsatilla Vulgaris 30X, Sanguinaria Canadensis 30X, Tabacum 30X.

PURPOSE

Uses: Temporarily relieves heartburn, nausea & vomiting.**

INDICATIONS AND USAGE

Uses: Temporarily relieves heartburn, nausea & vomiting.**

DOSAGE AND ADMINISTRATION

Directions: Adults & children above 12 years: 10 drops orally 3 times daily, or as directed by a health care professional.

WARNINGS:

*Consult a physician for use in children under 12 years of age.

* IF PREGNANT OR BREAST-FEEDING, ask a health care professional before use.

* KEEP OUT OF THE REACH OF CHILDREN. In case of overdose (or accidental ingestion) get medical help or contact a Poison Control Center right away.

WARNINGS:

*Consult a physician for use in children under 12 years of age.

* IF PREGNANT OR BREAST-FEEDING, ask a health care professional before use.

* KEEP OUT OF THE REACH OF CHILDREN. In case of overdose (or accidental ingestion) get medical help or contact a Poison Control Center right away.

* Do not use if TAMPER EVIDENT seal is broken or missing.

Inactive Ingredients: Ethyl Alcohol USP, Purified Water.

QUESTIONS

Questions & Comments? Natural Creations, Inc. / Woodbine, IA 51579 / 712-647-1600

REFERENCES

*The letters “HPUS” indicate the components in the product are officially monographed in the Homeopathic Pharmacopeia of the United States.

**Claims based on traditional homeopathic practice, not accepted medical evidence. Not FDA evaluated.

PACKAGE LABEL

NDC: 43406-0032-1

Nausea

Vomiting HP

HOMEOPATHIC

1 fl oz (30 mL) / 20% Alcohol